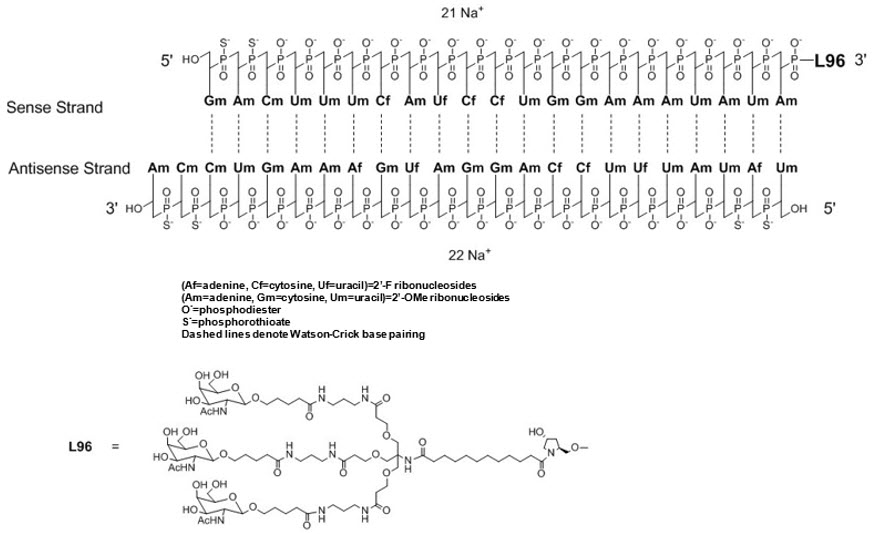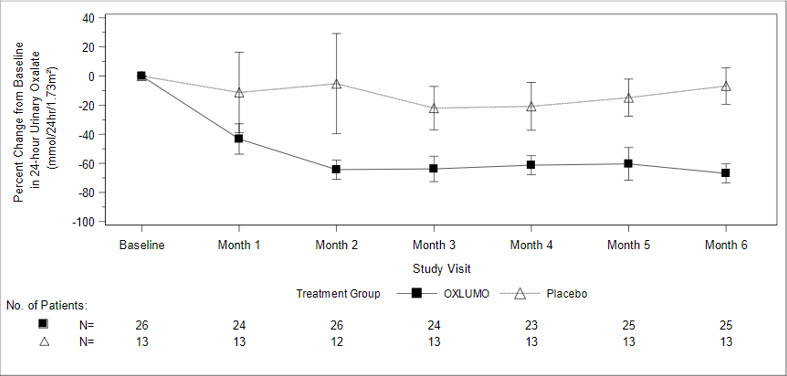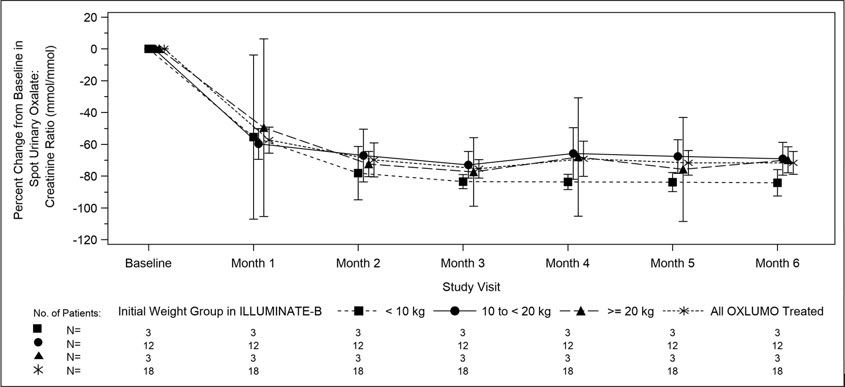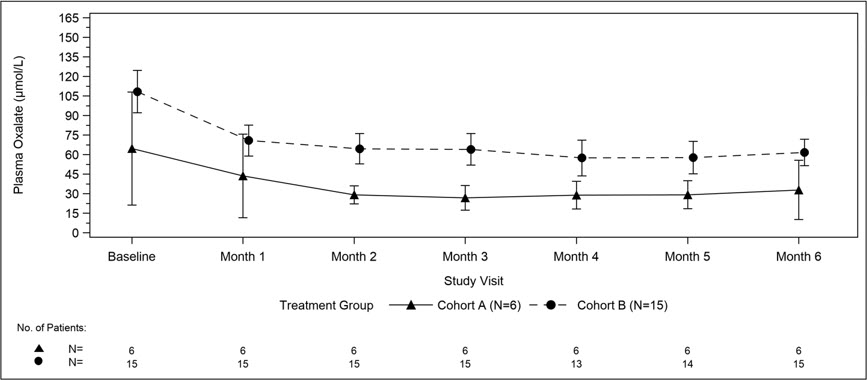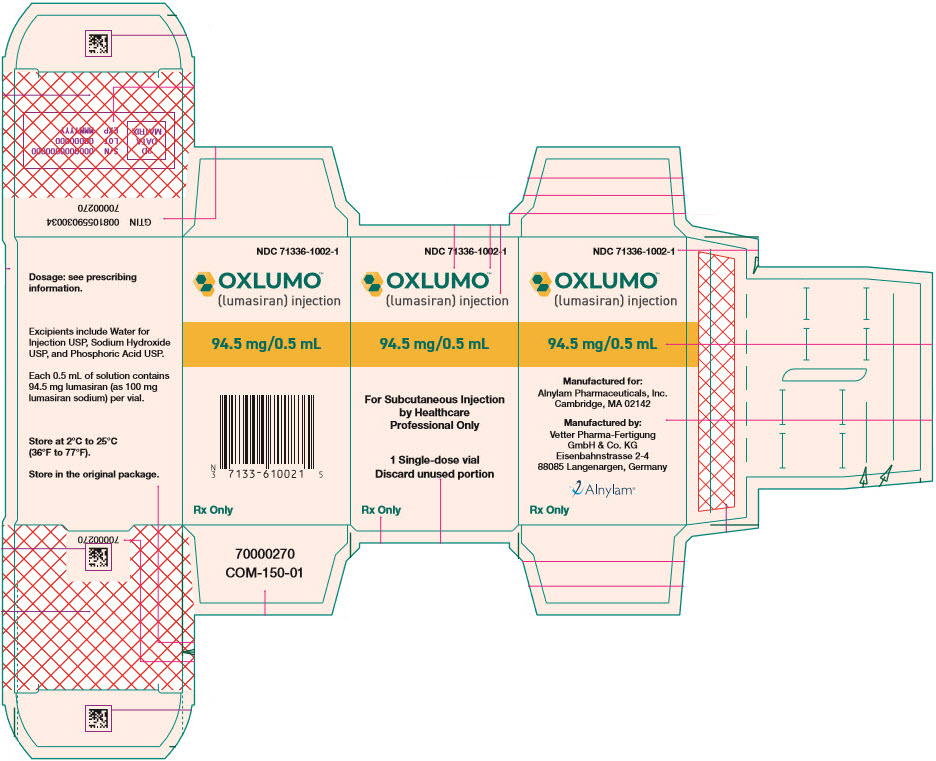 DRUG LABEL: OXLUMO
NDC: 71336-1002 | Form: INJECTION, SOLUTION
Manufacturer: Alnylam Pharmaceuticals, Inc.
Category: prescription | Type: HUMAN PRESCRIPTION DRUG LABEL
Date: 20251201

ACTIVE INGREDIENTS: lumasiran sodium 94.5 mg/0.5 mL
INACTIVE INGREDIENTS: water; Sodium hydroxide; Phosphoric acid

HIGHLIGHTS OF PRESCRIBING INFORMATION

These highlights do not include all the information needed to use OXLUMO® safely and effectively. See full prescribing information for OXLUMO.
OXLUMO (lumasiran) injection, for subcutaneous use
Initial U.S. Approval: 2020

1 INDICATIONS AND USAGE

OXLUMO is a HAO1-directed small interfering ribonucleic acid (siRNA) indicated for the treatment of primary hyperoxaluria type 1 (PH1) to lower urinary and plasma oxalate levels in pediatric and adult patients. (1)

2 DOSAGE AND ADMINISTRATION

- The recommended dose of OXLUMO by subcutaneous injection is based on body weight. (2.1)

Body Weight | Loading Dose | Maintenance Dose
less than 10 kg | 6 mg/kg once monthly for 3 doses | 3 mg/kg once monthly, beginning 1 month after the last loading dose
10 kg to less than 20 kg | 6 mg/kg once monthly for 3 doses | 6 mg/kg once every 3 months (quarterly), beginning 1 month after the last loading dose
20 kg and above | 3 mg/kg once monthly for 3 doses | 3 mg/kg once every 3 months (quarterly), beginning 1 month after the last loading dose

- See Full Prescribing Information for important preparation and administration instructions. (2.2)

3 DOSAGE FORMS AND STRENGTHS

- Injection: 94.5 mg/0.5 mL in a single-dose vial. (3)

4 CONTRAINDICATIONS

- None. (4)

6 ADVERSE REACTIONS

The most common adverse reaction (reported in ≥20% of patients) is injection site reactions. (6.1)

To report SUSPECTED ADVERSE REACTIONS, contact Alnylam Pharmaceuticals at 1-877-256-9526 or FDA at 1-800-FDA-1088 or www.fda.gov/medwatch.

FULL PRESCRIBING INFORMATION

1 INDICATIONS AND USAGE

OXLUMO is indicated for the treatment of primary hyperoxaluria type 1 (PH1) to lower urinary and plasma oxalate levels in pediatric and adult patients [see Clinical Pharmacology (12.1), Clinical Studies (14.1, 14.2, 14.3)].

2 DOSAGE AND ADMINISTRATION

2.1 Recommended Dosage

The recommended dosing regimen of OXLUMO consists of loading doses (monthly for 3 doses) followed by maintenance doses (beginning 1 month after the last loading dose) administered subcutaneously as shown in Table 1.

Dosing is based on actual body weight.

Table 1. OXLUMO Weight-Based Dosing Regimen
Body Weight | Loading Dose | Maintenance Dose
Less than 10 kg | 6 mg/kg once monthly for 3 doses | 3 mg/kg once monthly, beginning 1 month after the last loading dose
10 kg to less than 20 kg | 6 mg/kg once monthly for 3 doses | 6 mg/kg once every 3 months (quarterly), beginning 1 month after the last loading dose
20 kg and above | 3 mg/kg once monthly for 3 doses | 3 mg/kg once every 3 months (quarterly), beginning 1 month after the last loading dose

For Patients on Hemodialysis

Administer OXLUMO after hemodialysis if administered on dialysis days.

Missed Dose

If a dose is delayed or missed, administer OXLUMO as soon as possible. Resume prescribed monthly or quarterly dosing, from the most recently administered dose.

2.2 Administration Instructions

OXLUMO is intended for subcutaneous use and should be administered by a healthcare professional.

Visually inspect the drug product solution. Do not use if it contains particulate matter or if it is cloudy or discolored. OXLUMO is a sterile, preservative-free, clear, colorless-to-yellow solution. It is supplied in a single-dose vial, as a ready-to-use solution that does not require additional reconstitution or dilution prior to administration.

- Use aseptic technique.
- Divide injection volumes greater than 1.5 mL equally into multiple syringes.
- For volumes less than 0.3 mL, a sterile 0.3-mL syringe is recommended. If using a 0.3 mL (30 unit) insulin syringe, 1-unit markings indicate 0.01 mL.
- Administer subcutaneous injection into the abdomen, thigh, or the side or back of the upper arms. Rotate injection sites. Do not inject into scar tissue or areas that are reddened, inflamed, or swollen.
  - If injecting into the abdomen, avoid the area around the navel.
  - If more than one injection is needed for a single dose of OXLUMO, the injection sites should be at least 2 cm apart.
- Discard unused portion of the drug.

3 DOSAGE FORMS AND STRENGTHS

Injection: 94.5 mg/0.5 mL clear, colorless-to-yellow solution in a single-dose vial.

4 CONTRAINDICATIONS

None.

6 ADVERSE REACTIONS

6.1 Clinical Trials Experience

Because clinical trials are conducted under widely varying conditions, adverse reaction rates observed in the clinical trials of a drug cannot be directly compared to rates in the clinical trials of another drug and may not reflect the rates observed in practice.

The safety of OXLUMO has been evaluated in a placebo-controlled trial and two single-arm clinical trials. Across these trials, 98 patients with PH1 have been treated with OXLUMO, including 71 pediatric patients and 15 patients on hemodialysis. Overall, 92 patients were treated for at least 6 months, 78 patients for at least 12 months, and 29 patients for at least 24 months.

In the randomized, placebo-controlled, double-blind study ILLUMINATE-A in pediatric and adult patients with PH1 aged 6 to 61 years, 26 patients received OXLUMO, and 13 patients received placebo. Of these, 25 patients received ≥5 months of treatment.

In two single-arm studies in patients with PH1, ILLUMINATE-B (patients <6 years of age) and ILLUMINATE-C (pediatric and adult patients with moderately or severely reduced GFR [eGFR ≤45 mL/min/1.73 m^2 or pediatric patients <12 months of age with serum creatinine above the upper limit of normal for age] and patients with kidney failure on hemodialysis), the OXLUMO safety profile was similar to that seen in ILLUMINATE-A [see Clinical Studies (14)].

In placebo-controlled and open-label clinical studies the most common adverse reaction reported was injection site reaction. Injection site reactions included erythema, swelling, pain, hematoma, pruritus, and discoloration. These symptoms were generally mild and resolved within one day of the injection and did not lead to discontinuation of treatment.

Table 2. Adverse Reactions Reported in at Least 10% of Patients Treated with OXLUMO and that Occurred at Least 5% More Frequently than in Patients Treated with Placebo in ILLUMINATE-A during the 6-Month Double-Blind Period
Adverse Reaction | OXLUMO N=26 N (%) | Placebo N=13 N (%)
Injection site reaction | 10 (38) | 0 (0)
Abdominal pain [Grouped term includes abdominal pain, abdominal pain upper, abdominal pain lower, and abdominal discomfort.] | 4 (15) | 1 (8)

6.2 Postmarketing Experience

The following additional adverse reaction has been reported during post-approval use. Because these events are reported voluntarily from a population of uncertain size, it is generally not possible to reliably estimate their frequency.

Immune system disorder: Hypersensitivity

8 USE IN SPECIFIC POPULATIONS

8.1 Pregnancy

Risk Summary

There are no available data with the use of OXLUMO in pregnant women to evaluate a drug-associated risk of major birth defects, miscarriage, or adverse maternal or fetal outcomes.

No adverse effects on pregnancy or embryo-fetal development related to OXLUMO were observed in rats at 45 times and in rabbits at 90 times the maximum recommended human dose in women (see Data).

The estimated background risk of major birth defects and miscarriage in the indicated population is unknown. All pregnancies have a background risk of birth defect, loss, or other adverse outcomes. In the U.S. general population, the estimated background risk of major birth defects and miscarriage in clinically recognized pregnancies is 2% to 4% and 15% to 20%, respectively.

Data

Animal Data

In an embryo-fetal development study in pregnant rats, lumasiran was administered subcutaneously at doses of 3, 10, and 30 mg/kg/day during organogenesis (gestational days 6-17). Administration of lumasiran resulted in no effects on embryo-fetal survival or fetal body weights and no lumasiran-related fetal malformations were observed. The 30 mg/kg/day dose in rats is 45 times the maximum recommended human dose (MRHD) for women of 3 mg/kg/month normalized to 0.1 mg/kg/day, based on body surface area. In an embryo-fetal development study in female rabbits, lumasiran was administered subcutaneously at doses of 3, 10, and 30 mg/kg/day during organogenesis (gestational days 7-19). There were decreases in maternal food consumption and decreases in maternal body weight gains at doses ≥3 mg/kg/day. There were no lumasiran-related fetal findings identified at doses up to 30 mg/kg/day (90 times the normalized MRHD based on body surface area).

In a postnatal development study, lumasiran administered subcutaneously to pregnant female rats on gestational days 7, 13, 19 and on lactation days 6, 12, and 18 through weaning at doses up to 50 mg/kg did not produce maternal toxicity or developmental effects in the offspring.

8.2 Lactation

Risk Summary

There are no data on the presence of OXLUMO in human milk, the effects on the breastfed child, or the effects of the drug on milk production. The developmental and health benefits of breastfeeding should be considered along with the mother's clinical need for OXLUMO and any potential adverse effects on the breastfed child from OXLUMO or from the underlying maternal condition.

8.4 Pediatric Use

The safety and effectiveness of OXLUMO have been established in pediatric patients aged birth and older. Use of OXLUMO in these age groups is supported by evidence from an adequate and well controlled study of OXLUMO in pediatric patients 6 years or older and adults with PH1 (ILLUMINATE-A), a single-arm clinical study in pediatric patients less than 6 years of age with PH1 (ILLUMINATE-B), and a single-arm clinical study in pediatric and adult patients with PH1 who had advanced chronic kidney disease including patients on hemodialysis (ILLUMINATE-C) [see Adverse Reactions (6.1), Clinical Studies (14)].

8.5 Geriatric Use

Clinical studies of OXLUMO did not include sufficient numbers of patients aged 65 and over to determine whether they respond differently from younger patients.

8.6 Hepatic Impairment

No dose adjustment is recommended for patients with mild [total bilirubin > upper limit of normal (ULN) to 1.5 × ULN or AST > ULN] or moderate hepatic impairment (total bilirubin > 1.5 to 3 × ULN with any AST). OXLUMO has not been studied in patients with severe hepatic impairment (total bilirubin > 3 × ULN with any AST) [see Clinical Pharmacology (12.3)].

8.7 Renal Impairment

No dose adjustment is necessary in patients with renal impairment including patients with kidney failure treated with hemodialysis [see Clinical Pharmacology (12.3)]. OXLUMO has not been studied in patients on peritoneal dialysis.

11 DESCRIPTION

OXLUMO injection contains lumasiran, a HAO1-directed double-stranded small interfering ribonucleic acid (siRNA), covalently linked to a ligand containing N-acetylgalactosamine (GalNAc).

The structural formula of lumasiran sodium is presented below:

The molecular formula of lumasiran sodium is C530H669F10N173O320P43S6Na43 and the molecular weight is 17,286 Da.

OXLUMO is supplied as a sterile, preservative-free, clear, colorless-to-yellow solution for subcutaneous administration containing the equivalent of 94.5 mg of lumasiran (provided as lumasiran sodium) in 0.5 mL of water for injection and sodium hydroxide and/or phosphoric acid to adjust the pH to ~ 7.0.

12 CLINICAL PHARMACOLOGY

12.1 Mechanism of Action

Lumasiran reduces levels of glycolate oxidase (GO) enzyme by targeting the hydroxyacid oxidase 1 (HAO1) messenger ribonucleic acid (mRNA) in hepatocytes through RNA interference. Decreased GO enzyme levels reduce the amount of available glyoxylate, a substrate for oxalate production. As the GO enzyme is upstream of the deficient alanine: glyoxylate aminotransferase (AGT) enzyme that causes PH1, the mechanism of action of lumasiran is independent of the underlying AGXT gene mutation. OXLUMO is not expected to be effective in primary hyperoxaluria type 2 (PH2) or type 3 (PH3) because its mechanism of action does not affect the metabolic pathways causing hyperoxaluria in PH2 and PH3.

12.2 Pharmacodynamics

The pharmacodynamic effects of OXLUMO have been evaluated in adult and pediatric patients with PH1 across a range of doses and dosing frequency. Dose-dependent reductions in urinary oxalate levels were observed, resulting in the selection of the recommended body weight-based loading and maintenance dosing regimens. With the recommended dosing regimens, onset of effect was observed within two weeks after the first dose and maximal reductions in urinary oxalate were observed by Month 2 and persisted with continued use of OXLUMO maintenance dosage [see Figures 1 and 2 in Clinical Studies (14.1, 14.2)].

Cardiac Electrophysiology

At the recommended dose, OXLUMO does not lead to clinically relevant QT interval prolongation.

12.3 Pharmacokinetics

The pharmacokinetic (PK) properties of OXLUMO were evaluated following administration of single and multiple dosages in patients with PH1 as summarized in Table 3.

Table 3. Pharmacokinetic Parameters of Lumasiran
 |  | Lumasiran
General Information
Steady-State Exposure | Cmax [Median (Range)] | 462 (38.5 to 1500) ng/mL
Steady-State Exposure | AUC0-last [Median (Range)] | 6810 (2890 to 10700) ng∙h/mL
Dose Proportionality |  | - Lumasiran exhibited an approximately dose proportional increase in plasma exposure following single subcutaneous doses ranging from 0.3 to 6 mg/kg. - Lumasiran exhibited time-independent pharmacokinetics with multiple doses of 1 and 3 mg/kg once monthly or 3 mg/kg quarterly.
Accumulation |  | - No accumulation of lumasiran was observed in plasma after repeated monthly or quarterly dosing.
Absorption
Tmax [Median (Range)] |  | 4 (0.5 to 12) hours
Distribution [Lumasiran distributes primarily to the liver after subcutaneous administration. Cmax = maximum plasma concentration; AUC0-last = area under the plasma concentration-time curve from time of administration (0) to the last measurable time point (last); Tmax = time to maximum concentration; Vd/F = apparent volume of distribution; CV = coefficient of variation; CL/F = apparent clearance.]
Estimated Vd/F |  | 4.9 L
Protein Binding |  | 85%
Elimination
Apparent Half-Life [Mean (%CV)] |  | 5.2 (47%) hours
Estimated CL/F |  | 26.5 L/hour
Metabolism
Primary Pathway |  | Lumasiran is metabolized by endo- and exonucleases to oligonucleotides of shorter lengths.
Excretion
Primary Pathway |  | Less than 26% of the administered dose of lumasiran is excreted unchanged into the urine within 24 hours with the rest excreted as inactive metabolite.

Specific Populations

No clinically significant differences in the pharmacokinetics or pharmacodynamics of lumasiran were observed based on age (4 months to <65 years old), sex, race/ethnicity, renal impairment, use of hemodialysis, or mild to moderate hepatic impairment (total bilirubin ≤ ULN and AST > ULN; or total bilirubin ≤ 3× ULN). The effect of severe hepatic impairment on the pharmacokinetics of lumasiran is unknown.

Body Weight

In children <20 kg, lumasiran Cmax was twice as high due to the higher 6 mg/kg dose and faster absorption rate. At the approved recommended dosage, lumasiran AUC was similar across the 6.2 kg to 110 kg body weight range [see Dosage and Administration (2.1)].

Drug Interaction Studies

Clinical Studies

No clinical studies evaluating the drug interaction potential of lumasiran have been conducted. Concomitant use of pyridoxine (vitamin B6) did not influence the pharmacodynamics or pharmacokinetics of lumasiran.

In Vitro Studies

In vitro studies indicate that lumasiran is not a substrate or an inhibitor of cytochrome P450 (CYP) enzymes. Lumasiran is not expected to induce CYP enzymes or modulate the activities of drug transporters.

12.6 Immunogenicity

The observed incidence of anti-drug antibody (ADA, including neutralizing antibody) is highly dependent on the sensitivity and specificity of the assay. Differences in assay methods preclude meaningful comparisons of the incidence of ADA in the studies described below with the incidence of ADA in other studies, including those of OXLUMO or of other siRNA products.

Across all clinical studies in the lumasiran development program, including patients with PH1 and healthy volunteers dosed with OXLUMO, 7 of 120 (6%) lumasiran-treated individuals with mean follow-up duration of 8.9 months, tested positive for ADA, as early as from Day 29.

No clinically significant differences in the safety, pharmacokinetic, or pharmacodynamic profiles of lumasiran were observed in patients who tested positive for ADA.

13 NONCLINICAL TOXICOLOGY

13.1 Carcinogenesis, Mutagenesis, Impairment of Fertility

Carcinogenicity studies were conducted in Tg-rasH2 mice and Sprague Dawley rats.

Lumasiran was not carcinogenic in transgenic Tg-rasH2 mice following monthly subcutaneous administration of lumasiran for 26 weeks at doses of 150, 500, or 1500 mg/kg.

In a 2-year carcinogenicity study, lumasiran was not carcinogenic up to the highest dose tested. Sprague Dawley rats were administered subcutaneous doses of 20, 55, or 110 mg/kg lumasiran once every 4 weeks (3, 9, or 18 times the normalized maintenance MRHD, based on body surface area).

Lumasiran was not genotoxic in an in vitro bacterial reverse mutation (Ames) assay, in the in vitro chromosomal aberration assay in cultured human peripheral blood lymphocytes, or the in vivo micronucleus assay in rats.

Administration of lumasiran by weekly subcutaneous doses of 0, 5, 15, and 50 mg/kg in male and female rats prior to and during mating and continuing in females once on Day 6 of presumed gestation resulted in no adverse effects upon the male or female fertility endpoints evaluated.

14 CLINICAL STUDIES

14.1 ILLUMINATE-A

ILLUMINATE-A was a randomized, double-blind trial comparing lumasiran and placebo in 39 patients 6 years of age and older with PH1 and an eGFR ≥30 mL/min/1.73 m^2 (ILLUMINATE-A; NCT03681184). Patients received 3 loading doses of 3 mg/kg OXLUMO (N=26) or placebo (N=13) administered once monthly, followed by quarterly maintenance doses of 3 mg/kg OXLUMO or placebo [see Dosage and Administration (2.1)]. After six months, all patients received OXLUMO.

The median age of patients at first dose was 15 years (range 6 to 61 years), 67% were male, and 77% were White. At baseline, the median 24-hour urinary oxalate excretion corrected for body surface area (BSA) was 1.7 mmol/24 h/1.73 m^2, the median plasma oxalate level was 13.1 µmol/L, 33% of patients had eGFR ≥90 mL/min/1.73 m^2, 49% had eGFR of 60 to <90 mL/min/1.73 m^2, and 18% had eGFR 30 to <60 mL/min/1.73 m^2, 56% were on pyridoxine, and 85% reported a history of symptomatic kidney stone events.

The primary endpoint was the percent reduction from baseline in 24-hour urinary oxalate excretion corrected for BSA averaged over Months 3 through 6. The LS mean percent change from baseline in 24-hour urinary oxalate in the OXLUMO group was -65% (95% CI: -71, -59) compared with -12% (95% CI: -20, -4) in the placebo group, resulting in a between-group LS mean difference of 53% (95% CI: 45, 62; p<0.0001) [Figure 1].

Figure 1. ILLUMINATE-A: Percent Change from Baseline in 24-hour Urinary Oxalate by Month

Abbreviation: CI ꞊ Confidence Interval.
Results are plotted as mean (95% CI) of percent change from baseline.

By Month 6, 52% (95% CI: 31, 72) of patients treated with OXLUMO achieved a normal 24-hour urinary oxalate corrected for BSA (≤0.514 mmol/24 hr/1.73 m^2) compared to 0% (95% CI: 0, 25) placebo-treated patients (p=0.001). Reduced urinary oxalate levels were maintained through Month 24 in patients treated with OXLUMO.

14.2 ILLUMINATE-B

ILLUMINATE-B was a single-arm study in 18 patients <6 years of age with PH1 and an eGFR >45 mL/min/1.73 m^2 for patients ≥12 months of age or a normal serum creatinine for patients <12 months of age (ILLUMINATE-B; NCT03905694). Dosing was based on body weight [see Dosage and Administration (2.1)].

The median age of patients at first dose was 51 months (range 4 to 74 months), 56% were female, and 88% were White. Three patients were less than 10 kg, 12 were 10 kg to <20 kg, and 3 were ≥20 kg. The median spot urinary oxalate: creatinine ratio at baseline was 0.47 mmol/mmol.

The primary endpoint was the percent reduction from baseline in spot urinary oxalate: creatinine ratio averaged over Months 3 through 6. Patients treated with OXLUMO achieved a reduction in spot urinary oxalate: creatinine ratio from baseline of 72% (95% CI: 66, 78) (Figure 2). The reduction in urinary oxalate excretion was maintained with continued OXLUMO treatment through Month 12.

Figure 2. ILLUMINATE-B: Percent Change from Baseline in Spot Urinary Oxalate: Creatinine Ratio by Month

Abbreviation: CI ꞊ Confidence Interval.
Results are plotted as mean (95% CI) of percent change from baseline.

14.3 ILLUMINATE-C

A total of 21 patients were enrolled and treated with OXLUMO in a multi-center, single-arm study in patients with PH1 and an eGFR ≤45 mL/min/1.73 m^2 in patients 12 months of age and older or an elevated serum creatinine for age in patients less than 12 months of age, including patients on hemodialysis. ILLUMINATE-C included 2 cohorts. Cohort A included 6 patients who did not require dialysis at the time of study enrollment. Cohort B included 15 patients who were on a stable regimen of hemodialysis; the hemodialysis regimen was to remain stable in these patients for the first 6 months of the study. Patients received the recommended dosing regimen of OXLUMO based on body weight [see Dosage and Administration (2.1)]. Patients requiring peritoneal dialysis were excluded.

The median age of patients at first dose was 9 years (range 0 to 59 years), 57% were male, and 76% were White. For Cohort A, the median plasma oxalate level was 58 µmol/L. For Cohort B, the median pre-dialysis plasma oxalate level was 104 µmol/L.

The primary endpoint was the percent change in plasma oxalate from baseline to Month 6 (average from Month 3 to Month 6) for Cohort A (N=6) and the percent change in pre-dialysis plasma oxalate from baseline to Month 6 (average from Month 3 to Month 6) for Cohort B (N=15). The percent change from baseline to Month 6 in plasma oxalate levels in Cohort A was an LS mean difference of -33% (95% CI: -82, 15) and in Cohort B was -42% (95% CI: -51, -34).

Mean plasma oxalate decreased from 65 µmol/L (95% CI: 21, 108) at baseline to 33 µmol/L (95% CI: 10, 56) at Month 6 in Cohort A, and from 108 µmol/L (95% CI: 92, 125) at baseline to 62 µmol/L (95% CI: 51, 72) at Month 6 in Cohort B. The time course for changes in plasma oxalate is shown in Figure 3.

Figure 3. ILLUMINATE-C: Plasma Oxalate Levels (µmol/L) during the Primary Analysis Period by Month

Abbreviation: CI ꞊ Confidence Interval.
Results are plotted as mean (95% CI) of actual values.
For Cohort A, the baseline is defined as the mean of all plasma oxalate samples collected prior to the first dose of lumasiran;
for Cohort B, the baseline is defined as the last four pre-dialysis plasma oxalate samples collected prior to the first dose of lumasiran. In Cohort B, only pre-dialysis samples are utilized.

16 HOW SUPPLIED/STORAGE AND HANDLING

16.1 How Supplied

OXLUMO is a clear, colorless-to-yellow solution available in single-dose vials of 94.5 mg/0.5 mL in cartons containing one vial (NDC 71336-1002-1).

16.2 Storage and Handling

Store at 2°C to 25°C [36°F to 77°F].

Store OXLUMO in its original container until ready for use.

Manufactured for: Alnylam Pharmaceuticals, Inc., Cambridge, MA 02142

PRINCIPAL DISPLAY PANEL - 0.5 mL Vial Carton

NDC 71336-1002-1

OXLUMO™
(lumasiran) injection

94.5 mg/0.5 mL

For Subcutaneous Injection
by Healthcare
Professional Only

1 Single-dose vial
Discard unused portion

Rx Only